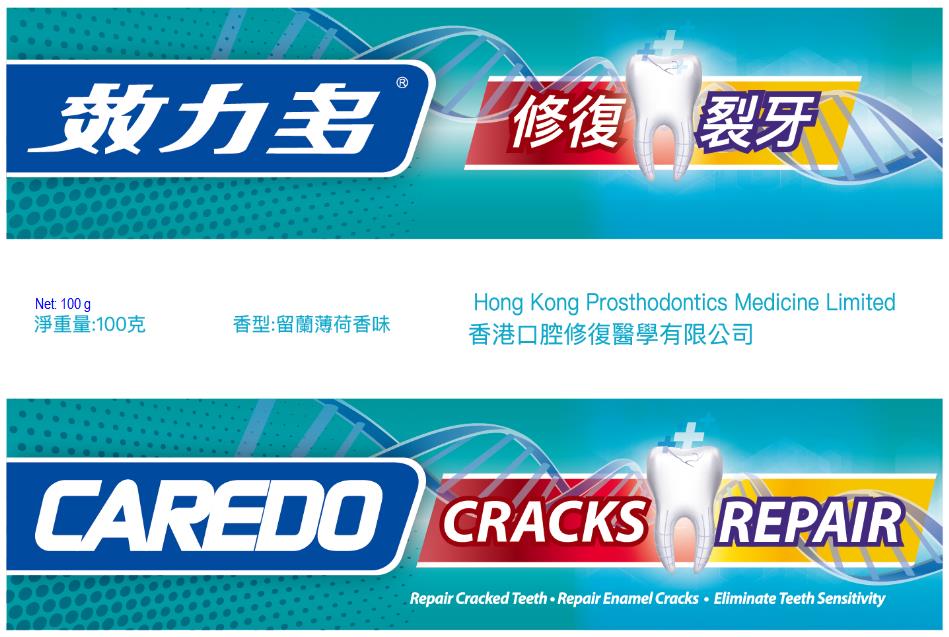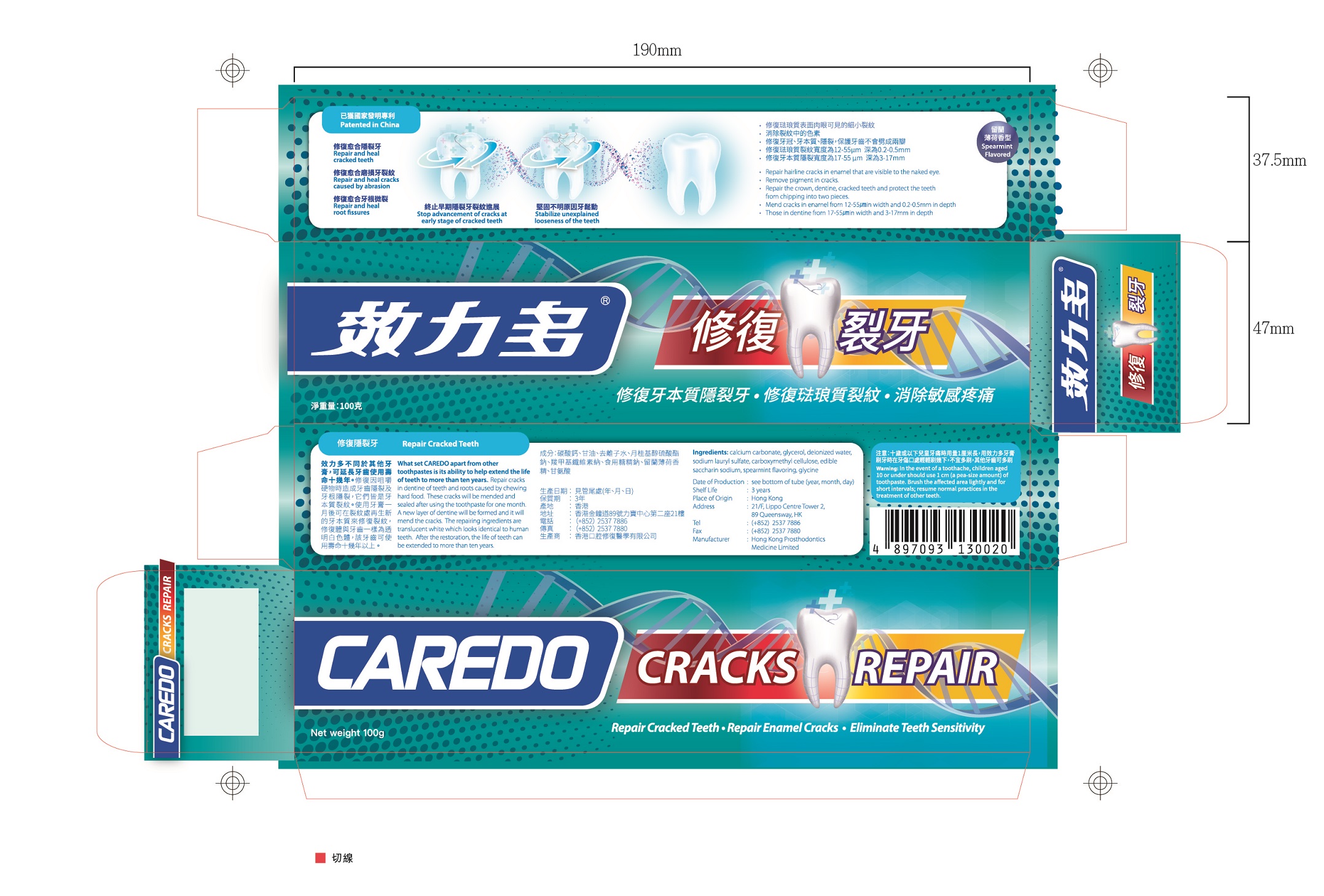 DRUG LABEL: CAREDO Repair Cracked Teeth Toothpastes
NDC: 72415-215 | Form: PASTE, DENTIFRICE
Manufacturer: Hong Kong Prosthodontics Medicine Limited
Category: otc | Type: HUMAN OTC DRUG LABEL
Date: 20180703

ACTIVE INGREDIENTS: GLYCINE 0.5 g/100 g
INACTIVE INGREDIENTS: CARBOXYMETHYLCELLULOSE 1 g/100 g; WATER 14.9 g/100 g; CALCIUM CARBONATE 50 g/100 g; SACCHARIN SODIUM 0.1 g/100 g; SODIUM LAURYL SULFATE 2 g/100 g; GLYCERIN 30 g/100 g; SPEARMINT OIL 1.5 g/100 g

CAREDO Repair Cracked Teeth Toothpaste, 100g

Active ingredient

glycine (0.5%): 0.5g/package.

Inactive ingredient

calcium carbonate (50%): 50g/package;

glycerol (30%): 30g/package;
deionized water (14.9%): 14.9g/package;
sodium lauryl sulfate (2%): 2g/package;
carboxymethyl cellulose (1%): 1g/package;
edible saccharin sodium (0.1%): 0.1g/package;
spearmint flavoring (1.5%): 1.5g/package;

Purpose

Repair and heal cracked teeth, cracks caused by abrasion, root fissures, etc.

When using

When tooth occurs cracked, cracks caused by abrasion, or root fissures, etc..

Do not use when oral infection.
It should be cautiously used if you are kind of allergic constitution or you have inflammation.

Stop use

If irritation or discomfort occurs, discontinue the use and consult a physician.

Ask doctor

If irritation or discomfort occurs, discontinue the use and consult a physician.

Ask doctor/pharmacist when you current use other drugs.

Keep out of reach of children

Questions

Please contact us when you have any questions.

Pregnancy or breast feeding

Pregnant or breast feeding women shall follow doctor advice.

Indications & usage

Apply properly this product on the toothbrush, and brush tooth as like common do.

Dosage & administration

One tube of 100g in one package.

Dosage forms & strengths

It is paste form.
Apply proper as you need.

Warnings

In the event of a toothache, children aged 10 or under should use 1cm (a pea-size amount) of toothpaste. Brush the affected area lightly and for short intervals; resume normal practices in the treatment of other teeth.

Package label. Principal display panel

---

Container Label

---

---

Package Label

---